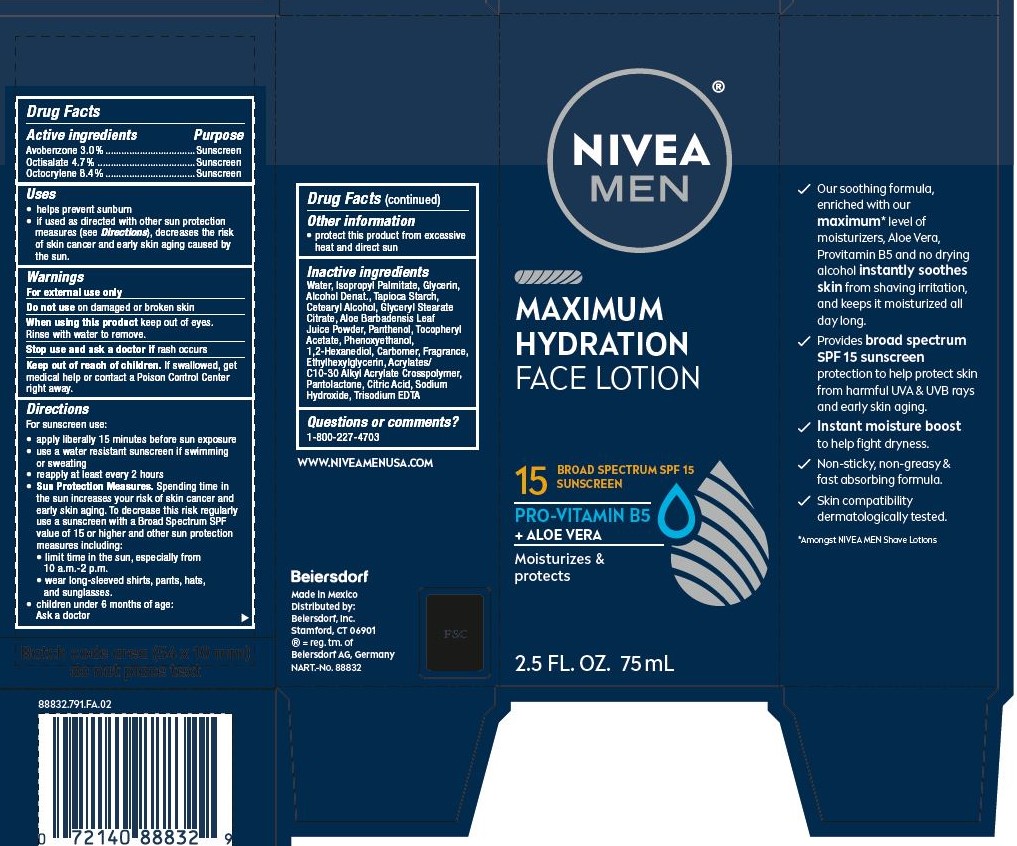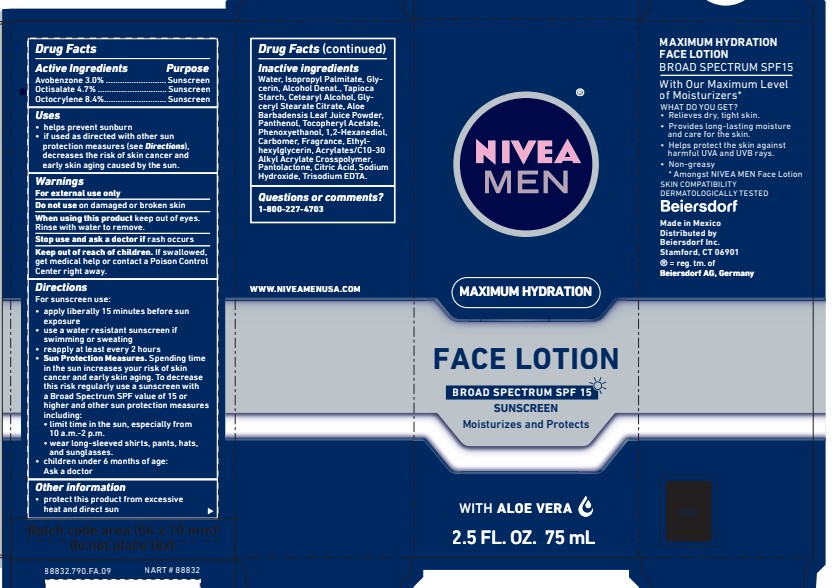 DRUG LABEL: Nivea Men Maximum Hydration Face
NDC: 10356-567 | Form: LOTION
Manufacturer: Beiersdorf Inc
Category: otc | Type: HUMAN OTC DRUG LABEL
Date: 20251231

ACTIVE INGREDIENTS: AVOBENZONE 3 g/100 mL; OCTISALATE 4.7 g/100 mL; OCTOCRYLENE 8.4 g/100 mL
INACTIVE INGREDIENTS: PHENOXYETHANOL; 1,2-HEXANEDIOL; ETHYLHEXYLGLYCERIN; CARBOMER INTERPOLYMER TYPE A (ALLYL SUCROSE CROSSLINKED); EDETATE TRISODIUM; SODIUM HYDROXIDE; CARBOMER HOMOPOLYMER TYPE C (ALLYL PENTAERYTHRITOL CROSSLINKED); WATER; GLYCERIN; ALCOHOL; ISOPROPYL PALMITATE; STARCH, TAPIOCA; CETOSTEARYL ALCOHOL; GLYCERYL STEARATE CITRATE; .ALPHA.-TOCOPHEROL ACETATE, DL-; ALOE; CITRIC ACID MONOHYDRATE; PANTOLACTONE; PANTHENOL

Nivea Men Maximum Hydration Face Lotion

Active ingredients

Avobenzone 3%

Octisalate 4.7%

Octocrylene 8.4%

Purpose
Sunscreen

Uses
• helps prevent sunburn
• if used as directed with other sun protection measures (see Directions),
decreases the risk of skin cancer and early skin aging caused by the sun.

Warnings
For external use only

Do not use on damaged or broken skin

When using this product keep out of eyes.
Rinse with water to remove.

Stop use and ask a doctor if rash occurs

Keep out of reach of children. If swallowed,
get medical help or contact a Poison Control
Center right away.

Questions or comments?
1-800-227-4703

Directions
For sunscreen use:
• apply liberally 15 minutes before sun exposure
• use a water resistant sunscreen if swimming or sweating
• reapply at least every 2 hours
• Sun Protection Measures. Spending time in the sun increases your risk of skin
cancer and early skin aging. To decrease this risk regularly use a sunscreen with
a Broad Spectrum SPF value of 15 or higher and other sun protection
measures including: • limit time in the sun, especially from
10 a.m.-2 p.m. • wear long-sleeved shirts, pants, hats, and sunglasses.
• children under 6 months of age: Ask a doctor

Inactive ingredients:

Water, Isopropyl Palmitate, Glycerin, Alcohol Denat.,

Tapioca Starch, Cetearyl Alcohol, Glyceryl

Stearate Citrate, Aloe Barbadensis Leaf Juice

Powder, Panthenol, Tocopheryl Acetate,

Phenoxyethanol, 1,2-Hexanediol,

Carbomer, Fragrance, Ethylhexylglycerin,

Acrylates/C10-30 Alkyl Acrylate

Crosspolymer, Pantolactone, Citric Acid, Sodium Hydroxide,

Trisodium EDTA.

PACKAGE LABEL

NIVEA MEN

Maximum Hydration Face Lotion

Broad Spectrum SPF 15
Sunscreen

with Pro-vitamin B5 and

Aloe Vera

Moisturizes and Protects

NIVEA MEN

Maximum Hydration Face Lotion

Broad Spectrum SPF 15
Sunscreen

Moisturizes and Protects

with Aloe Vera